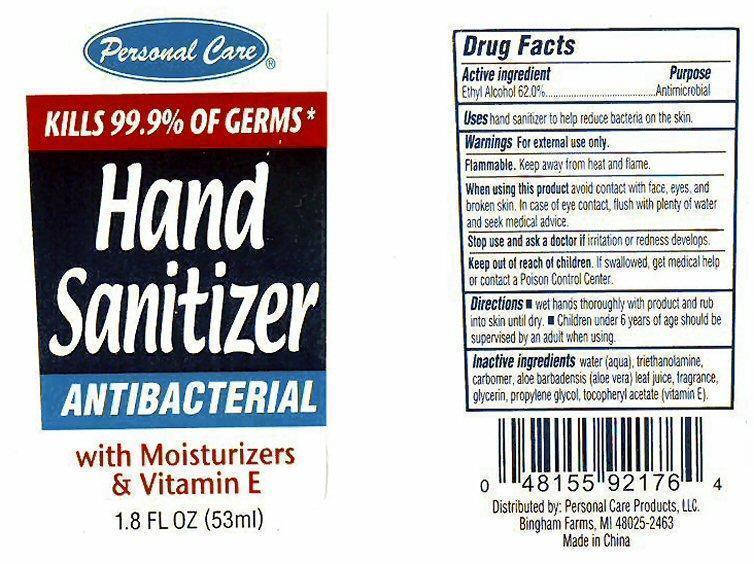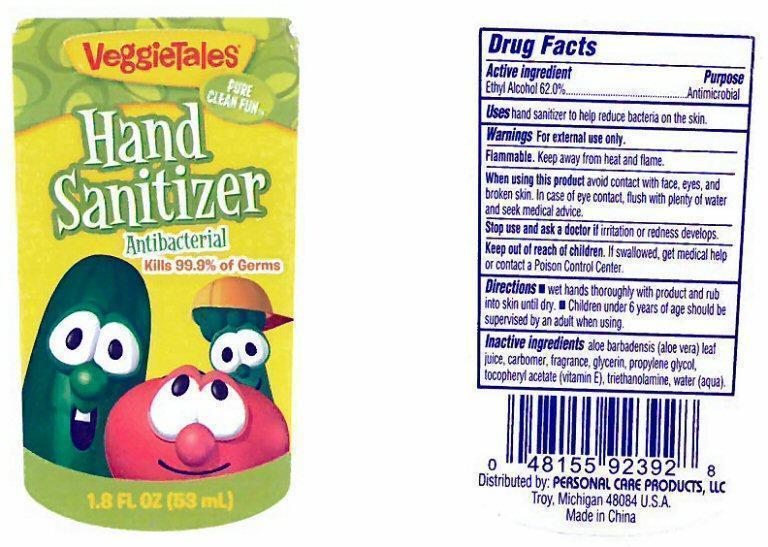 DRUG LABEL: Personal Care
                        
                        
NDC: 29500-9085 | Form: GEL
Manufacturer: Personal Care Products, Inc.
Category: otc | Type: HUMAN OTC DRUG LABEL
Date: 20130708

ACTIVE INGREDIENTS: ALCOHOL 0.62 mL/1 mL
INACTIVE INGREDIENTS: ALOE VERA LEAF; CARBOMER HOMOPOLYMER TYPE C; GLYCERIN; PROPYLENE GLYCOL; ALPHA-TOCOPHEROL ACETATE; TROLAMINE; WATER

Active Ingredient

Drug Facts
Ethyl Alcohol 62.0 %

Purpose

Antimicrobial

Uses

Uses hand sanitizer to help reduce bacteria on the skin.

Keep out of reach of children. If swallowed, get medical help or contact a Poison Control Center.

Directions

- wet hands thoroughly with product and rub into skin until dry.

- Children under 6 years of age should be supervised by an adult using this product.

Warnings When using this product Stop use

For external use only.

Flammable. Keep away from heat and flame.

When using this product avoid contact with face, eyes, and broken skin. In case of eye contact, flush with plenty of water and seek medical advice.

Stop use and ask a doctor if irritation or redness develops.

Inactive Ingredients

water (aqua), triethanolamine, carbomer, aloe barbadensis (aloe vera) leaf juice, fragrance, glycerin, propylene glycol, tocopheryl acetate (vitamin E).

Personal Care Hand Sanitizer

Personal Care®
KILLS 99.9% OF GERMS*
Hand Sanitizer
ANTIBACTERIAL
with Moisturizers and Vitamin E
1.8 FL OZ (53 ml)
Distributed by: Personal Care Products, LLC
Bingham Farms, MI 48025-2463
Made in China

VeggieTales Hand Sanitizer

VeggieTales
PURE CLEAN FUN
Hand Sanitizer
Antibacterial
Kills 99.9% of Germs
1.8 FL OZ (53 ml)
Distributed by: Personal Care Products, LLC
Bingham Farms, MI 48025-2463
Made in China